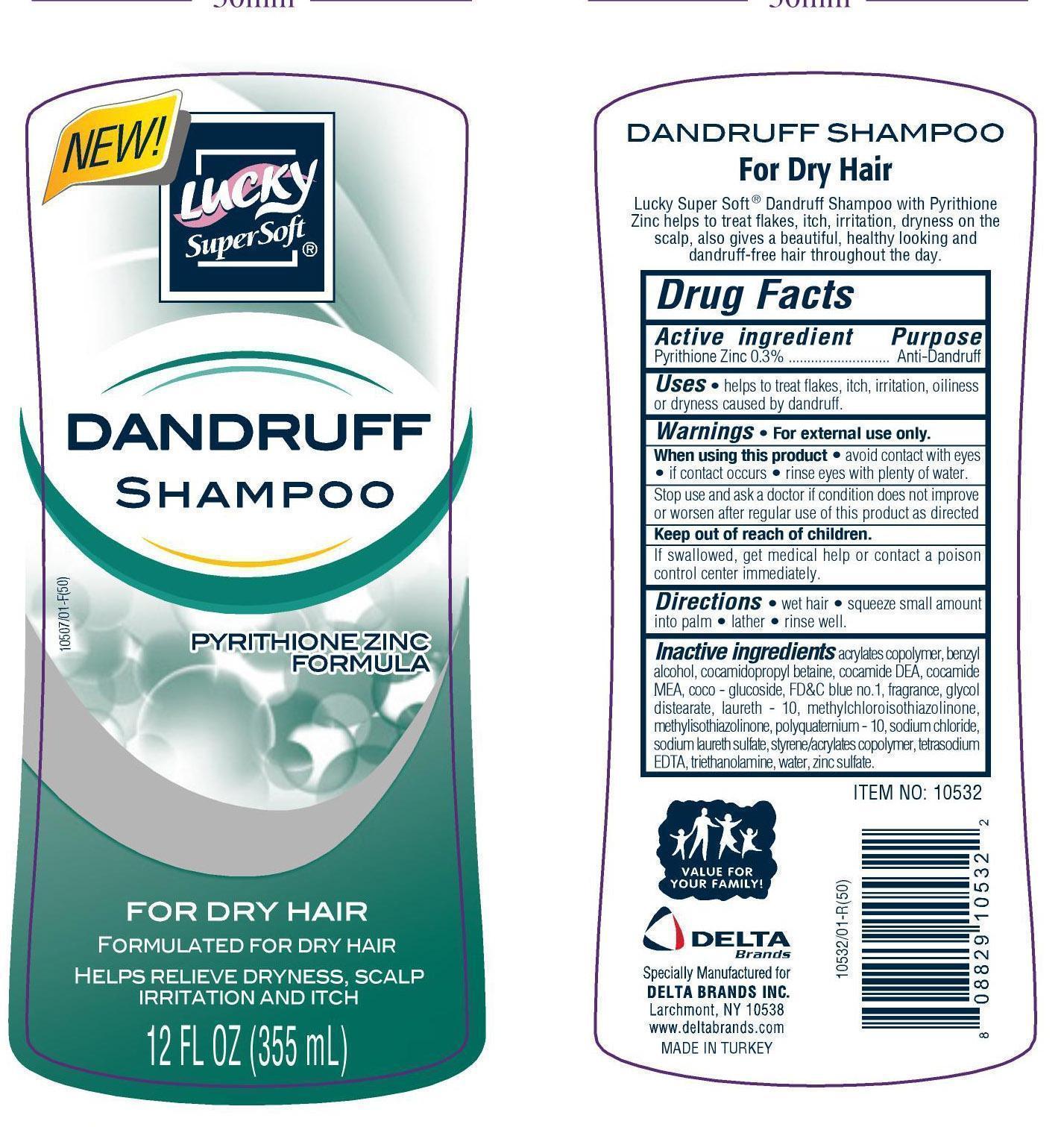 DRUG LABEL: Lucky
NDC: 20276-047 | Form: SHAMPOO
Manufacturer: Delta Brands Inc
Category: otc | Type: HUMAN OTC DRUG LABEL
Date: 20230622

ACTIVE INGREDIENTS: PYRITHIONE ZINC 0.3 g/100 mL
INACTIVE INGREDIENTS: BENZYL ALCOHOL; COCAMIDOPROPYL BETAINE; COCO DIETHANOLAMIDE; COCO MONOETHANOLAMIDE; COCO GLUCOSIDE; FD&C BLUE NO. 1; GLYCOL DISTEARATE; LAURETH-10; METHYLCHLOROISOTHIAZOLINONE; METHYLISOTHIAZOLINONE; POLYQUATERNIUM-10 (400 CPS AT 2%); SODIUM CHLORIDE; SODIUM LAURETH SULFATE; EDETATE SODIUM; TROLAMINE; WATER; ZINC SULFATE

ClsscpyrithioneShmpooDlta

Active Ingredient

Pyrithione zinc 0.3%

Purpose

Anti-dandruff

Uses

• helps to treat flakes, itch, irritation, oilness or dryness caused by dandruff.

Warnings

For external use only

When using this product

•avoid contact with eyes • if contact occurs, rinse eyes with plenty of water.

Stop use and ask a doctor

if condition does not improve or worsen after regular use of this product as directed

Keep out of reach of children

Keep this and all drugs out of reach of children If swallowed get medical help or contact a Poison Control Center right away.

Directions

•wet hair, •squeeze small amount into palm •lather, •rinse well

Inactive Ingredients

acrylates copolymer, benzyl alcohol, cocamidopropyl betaine, cocamide DEA, cocamide MEA, coco glucoside, FDC blue no. 1, fragrance, glycol distearate, laureth 10, methylchloroisothiazolinone, methylisothiazolinone,polyquarternium 10, sodium chloride, sodium laureth sulfate, styrene/acrylates copolymer, tetrasodium EDTA, triethanolamine, water, zinc sulfate